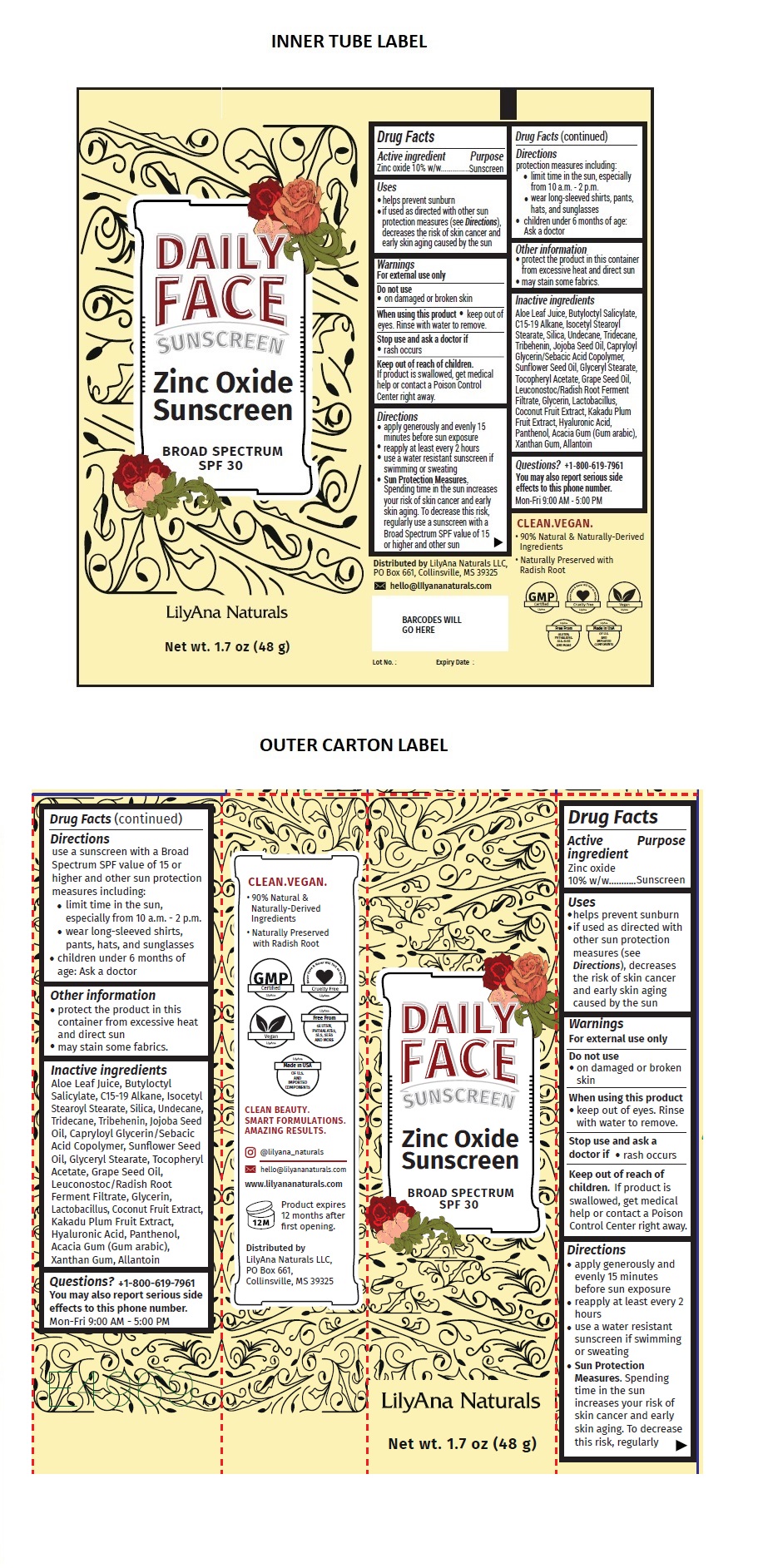 DRUG LABEL: DAILY FACE SUNSCREEN
NDC: 81781-101 | Form: CREAM
Manufacturer: Lilyana Naturals LLC
Category: otc | Type: HUMAN OTC DRUG LABEL
Date: 20210708

ACTIVE INGREDIENTS: ZINC OXIDE 10 g/100 g
INACTIVE INGREDIENTS: ALOE VERA LEAF; BUTYLOCTYL SALICYLATE; C15-19 ALKANE; ISOCETYL STEAROYL STEARATE; SILICON DIOXIDE; UNDECANE; TRIDECANE; TRIBEHENIN; JOJOBA OIL; CAPRYLOYL GLYCERIN/SEBACIC ACID COPOLYMER (2000 MPA.S); SUNFLOWER OIL; GLYCERYL MONOSTEARATE; .ALPHA.-TOCOPHEROL ACETATE; GRAPE SEED OIL; LEUCONOSTOC/RADISH ROOT FERMENT FILTRATE; GLYCERIN; LACTOBACILLUS ACIDOPHILUS; COCONUT; KAKADU PLUM; HYALURONIC ACID; PANTHENOL; ACACIA; XANTHAN GUM; ALLANTOIN

DAILY FACE Zinc Oxide Sunscreen BROAD SPECTRUM SPF 30

Active ingredient

Zinc oxide 10% w/w

Purpose

Sunscreen

Uses

- helps prevent sunburn
- if used as directed with other sun protection measures (see Directions), decreases the risk of skin cancer and early skin aging caused by the sun

Warnings

For external use only

Do not use

- on damaged or broken skin

When using this product

- keep out of eyes. Rinse with water to remove.

Stop use and ask a doctor if

- rash occurs

Keep out of reach of children. If product is swallowed, get medical help or contact a Poison Control Center right away.

Directions

• apply generously and evenly 15 minutes before sun exposure
• reapply at least every 2 hours
• use a water resistant sunscreen if swimming or sweating
• Sun Protection Measures. Spending time in the sun increases your risk of skin cancer and early skin aging. To decrease this risk, regularly use a sunscreen with a Broad Spectrum SPF value of 15 or higher and other sun protection measures including:
• limit time in the sun, especially from 10 a.m. - 2 p.m.
• wear long-sleeved shirts, pants, hats, and sunglasses
• children under 6 months of age: Ask a doctor

Other information

- protect the product in this container from excessive heat and direct sun
- may stain some fabrics.

Inactive ingredients

Aloe Leaf Juice, Butyloctyl Salicylate, C15-19 Alkane, Isocetyl Stearoyl Stearate, Silica, Undecane, Tridecane, Tribehenin, Jojoba Seed Oil, Capryloyl Glycerin/Sebacic Acid Copolymer, Sunflower Seed Oil, Glyceryl Stearate, Tocopheryl Acetate, Grape Seed Oil, Leuconostoc/Radish Root Ferment Filtrate, Glycerin, Lactobacillus, Coconut Fruit Extract, Kakadu Plum Fruit Extract, Hyaluronic Acid, Panthenol, Acacia Gum (Gum arabic), Xanthan Gum, Allantoin

Questions?

+1-800-619-7961
You may also report serious side effects to this phone number.
Mon-Fri 9:00 AM - 5:00 PM

CLEAN.VEGAN.
• 90% Natural & Naturally-Derived Ingredients
• Naturally Preserved with Radish Root

CLEAN BEAUTY.
SMART FORMULATIONS.
AMAZING RESULTS.

Lot No. :
Expiry Date :

@lilyana_naturals
hello@lilyananaturals.com

www.lilyananaturals.com

Product expires 12 months after first opening.

Distributed by
LilyAna Naturals LLC, PO Box 661,
Collinsville, MS 39325